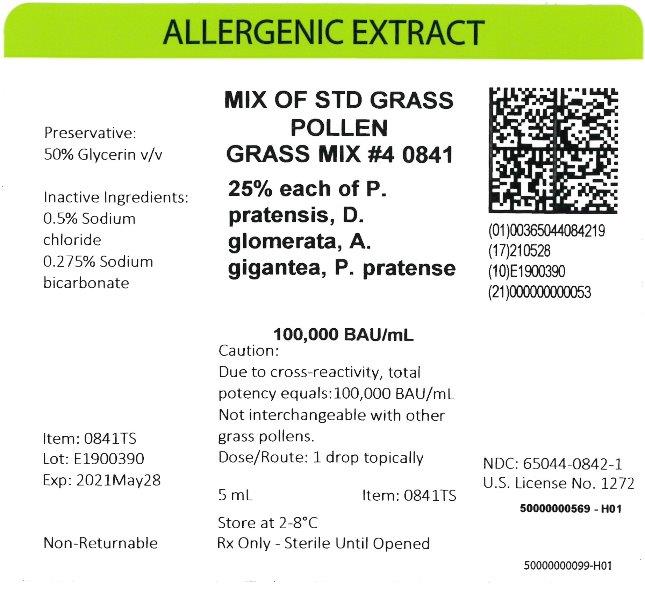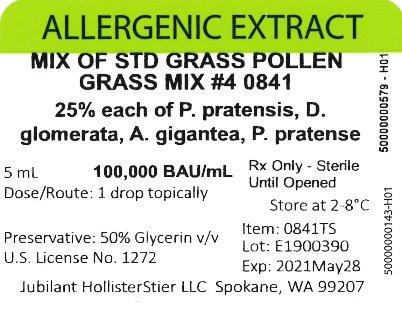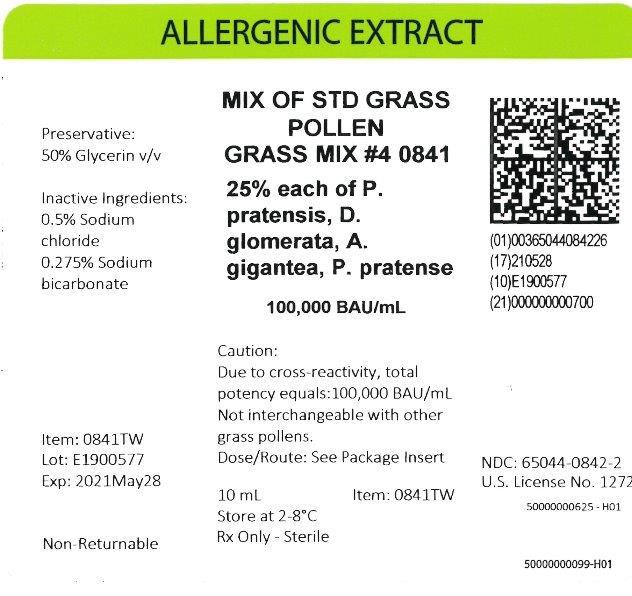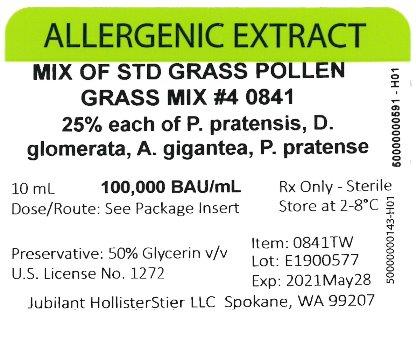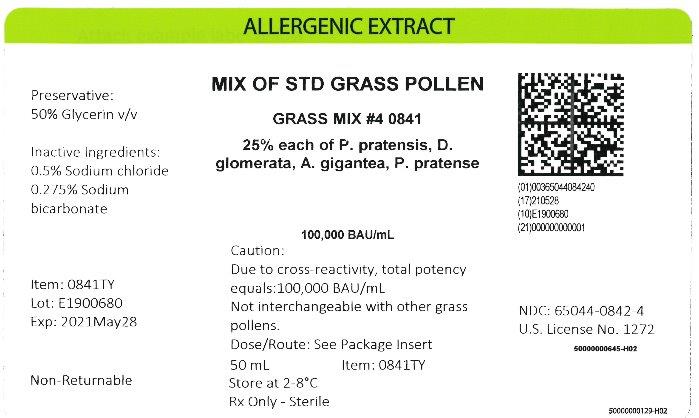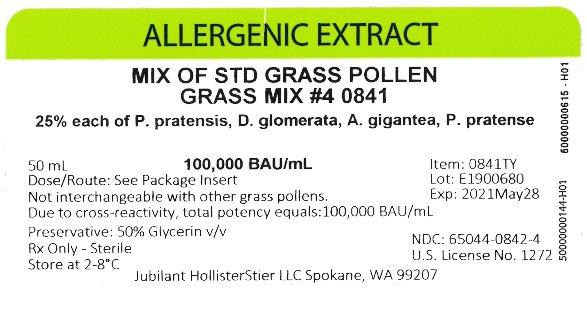 DRUG LABEL: Standardized Grass Pollen, Grass Mix 4
NDC: 65044-0842 | Form: INJECTION, SOLUTION
Manufacturer: Jubilant HollisterStier LLC
Category: other | Type: STANDARDIZED ALLERGENIC
Date: 20251119

ACTIVE INGREDIENTS: POA PRATENSIS POLLEN 25000 [BAU]/1 mL; DACTYLIS GLOMERATA POLLEN 25000 [BAU]/1 mL; AGROSTIS GIGANTEA POLLEN 25000 [BAU]/1 mL; PHLEUM PRATENSE POLLEN 25000 [BAU]/1 mL
INACTIVE INGREDIENTS: GLYCERIN; SODIUM CHLORIDE; SODIUM BICARBONATE

ALLERGENIC EXTRACTS STANDARDIZED GRASS POLLEN (glycerinated)

WARNINGS

This product is intended for use only by licensed medical personnel experienced in administering allergenic extracts and trained to provide immediate emergency treatment in the event of a life-threatening reaction.

Allergenic extracts may potentially elicit a severe life-threatening systemic reaction, rarely resulting in death 1. Therefore, emergency measures and personnel trained in their use must be available immediately in the event of such a reaction. Patients should be instructed to recognize adverse reaction symptoms and cautioned to contact the physician's office if symptoms occur. See ADVERSE REACTION, Section 3, of this insert for information regarding adverse event reporting.
Standardized glycerinated extracts may differ in potency from regular extracts and therefore, are not directly interchangeable with non-standardized extracts, or other manufacturers' products.
Note: BAU/mL Standardized grass pollens are not interchangeable with any other grass pollen products. This product should never be injected intravenously. Patients with cardiovascular diseases or pulmonary diseases such as symptomatic unstable, steroid-dependent asthma, and/or those who are receiving cardiovascular drugs such as beta blockers, may be at higher risk for severe adverse reactions. These patients may also be more refractory to the normal allergy treatment regimen. Patients should be treated only if the benefit of treatment outweighs the risks.1
Refer also to the CONTRAINDICATIONS, WARNINGS, PRECAUTIONS, ADVERSE REACTIONS and OVERDOSE Sections for further discussion.

DESCRIPTION

The grass pollens available in standardized form are: Bermuda Grass (Cynodon dactylon), Orchard Grass (Dactylis glomerata), Perennial Ryegrass (Lolium perenne), Timothy Grass (Phleum pratense), Redtop Grass (Agrostis alba), Kentucky Bluegrass (Poa pratensis), Meadow Fescue (Festuca elatior), and Sweet Vernalgrass (Anthoxanthum odoratum). The pollen extracts are intended for subcutaneous injection for immunotherapy; and intradermal and prick or puncture for diagnosis. Pollen extracts are sterile solutions containing the extractables of pollens, 0.5% Sodium Chloride, 0.275% Sodium Bicarbonate, and 50% Glycerin by volume as a preservative. Sterile, diluted Standardized Grass Pollen Extracts available for intradermal testing contain 0.9% sodium chloride, not more than 0.5% glycerin by volume, 0.03% sodium bicarbonate, and 0.4% phenol as a preservative. Source material for the extracts is collected using techniques such as water set or vacuuming. Source material for allergenic extracts contains no more than a total of 1% of detectable foreign materials (99% pollen purity). Note: BAU/mL Standardized grass pollens are not interchangeable with any other grass pollen products.

Product Concentration:
1. Bioequivalent Allergy Units. These allergenic extracts are labeled in Bioequivalent Allergy Units/mL (BAU/mL) based on their comparison (by ELISA Competition) to Center for Biologics Evaluation and Research (CBER), Food and Drug Administration (FDA) Reference Preparations.2 The FDA reference extracts have been assigned Bioequivalent Allergy Units based on the CBER ID50EAL method.5 Briefly, highly sensitive patients are skin tested to the reference preparation using an intradermal technique employing 3-fold extract dilutions. Depending on the dilution which elicits a summation of erythema diameter of 50mm (D50), Bioequivalent Allergy Units are assigned as follows:

BAU/mL | Intradermal Mean Dilution | D50
1000,000 | 1:5,000,000 | 13-14.9
10,000 | 1:500,000 | 11-12.9
1,000 | 1:50,000 | 9-10.9

The vial potency of Mixtures of Standardized Grasses is calculated by summation of the BAU/mL values of the components of the ingredient list which expresses the potency of each component per mL of the mixture.

2. Concentrate.
a. Concentrate label terminology applies to allergenic extract Custom Mixtures where the individual allergens being combined vary in strength or the designation of strength.

e.g. | Concentrate
50% | Short Ragweed 1:20 w/v
25% | Kentucky Bluegrass 100,000 BAU/mL
25% | Std. Mite D. farinae 10,000 AU/mL

Should the physician choose to calculate the actual strength of each component in the "Concentrate" mixture, the following formulation may be used:

Actual Allergen Strength in Concentrate Mixture | = | Allergen Manufacturing Strength | x | Allergen in Formulation (by volume or parts)

b. In the list of components portion of the product label for Stock Mixtures Containing Standardized Grasses, the potency of each component is calculated to express the potency of each component per 1 mL of the mixture. Vial potency is expressed as concentrate, or as a volume/volume dilution of concentrate.

CLINICAL PHARMACOLOGY

20

The mechanisms by which hyposensitization is achieved are not completely understood. It has been shown that repeated injections of appropriate allergenic extracts will ameliorate the intensity of allergic symptoms upon contact with the allergen.6, 7, 8, 9 Clinical studies which address the efficacy of immunotherapy are available. The allergens which have been studied are cat, mite, and some pollen extracts.10, 11, 12, 13, 14, 15
IgE antibodies bound to receptors on mast cell membranes are required for the allergic reaction, and their level is probably related to serum IgE concentrations. Immunotherapy has been associated with decreased levels of IgE, and also with increases in allergen specific IgG "blocking" antibody.
The histamine release response of circulating basophils to a specific allergen is reduced in some patients by immunotherapy, but the mechanism of this change is not yet clear.
The relationships among changes in blocking antibody, reaginic antibody, and mediator-releasing cells, and successful immunotherapy need study and clarification.
The CBER has evaluated the potency of eight grass pollen extract reference preparations and assigned potency units (BAU/mL) to each.5 The CBER clinical results follow in Table 1. Puncture data were obtained using a bifurcated needle.
Table 1
PUNCTURE AND INTRADERMAL DATA WITH CBER GRASS REFERENCES 3
A. Puncture Data with 10,000 BAU/mL Grass Extracts

 | Sum of Erythema (mm) | Sum of Wheal (mm)
Reference Pollen | N | Mean | Range | Mean | Range
Bermuda Grass - Cynodon dactylon | 15 | 90.3 | 43-123 | 15.7 | 7-31
Kentucky Bluegrass (June) - Poa pratensis | 15 | 77.3 | 47-107 | 15.9 | 6-28
Meadow Fescue - Festuca elatior | 15 | 81.1 | 57-115 | 11.9 | 7-22
Orchard Grass - Dactylis glomerata | 15 | 84.3 | 57-111 | 14.1 | 9-19
Perennial Ryegrass - Lolium perenne | 15 | 92.3 | 73-135 | 17.5 | 6-36
Redtop - Agrostis gigantea (alba) | 15 | 77.1 | 42-98 | 14.1 | 8-19
Sweet Vernalgrass - Anthoxanthum odoratum | 15 | 81.2 | 28-123 | 15.7 | 8-30
Timothy - Phleum pratense | 15 | 88.3 | 51-109 | 16.9 | 8-40

B. Intradermal Dose of CBER Grass References for 50mm Sum of Erythema (BAU50)

Reference Pollen | Mean | BAU50/mL Range
Bermuda Grass - Cynodon dactylon | 0.02 | 0.4-0.0003
Kentucky Bluegrass (June) - Poa pratensis | 0.02 | 0.1-0.004
Meadow Fescue - Festuca elatior | 0.02 | 0.9-0.002
Orchard Grass - Dactylis glomerata | 0.02 | 1.9-0.002
Perennial Ryegrass - Lolium Perenne | 0.02 | 0.7-0.002
Redtop - Agrostis gigantea (alba) | 0.02 | 0.8-0.004
Sweet Vernalgrass - Anthoxanthum odoratum | 0.02 | 1.0-0.002
Timothy - Phleum pratense | 0.02 | 0.6-0.002

TABLE 2

RELATIVE POTENCY OF PREVIOUSLY MANUFACTURED AND DISTRIBUTED NON-STANDARDIZED GRASSES TO CBER REFERENCE STANDARDS
Glycerinated (1:20 w/v) and Non-Glycerinated Pollen Extracts (1:10 w/v)

# of Jubilant HollisterStier LLC Lots Relative to the CBER Reference*
Pollen | # of Lots Tested | Less than | Equal to | Greater Than | Calculated BAU/mL Range** (Rounded to the nearest 000)
Orchard Grass | 20 | 2 | 13 | 5 | 66,000 - 242,000
Perennial Ryegrass | 17 | 5 | 12 | 0 | 25,000 - 127,000
Sweet Vernalgrass | 13 | 1 | 12 | 0 | 73,000 - 110,000
Kentucky Bluegrass | 21 | 8 | 12 | 1 | 32,000 - 145,000
Redtop | 20 | 5 | 6 | 9 | 13,000 - 402,000
Meadow Fescue | 21 | 0 | 1 | 20 | 128,000 - 948,000
Bermuda Grass | 22 | 3 | 13 | 6 | 6,000 - 28,000
Timothy | 19 | 11 | 6 | 2 | 43,000 - 176,000

*All CBER reference extracts contain 100,000 BAU/mL except Bermuda Grass which contains 10,000 BAU/mL.
**BAU/mL ranges between 69,990 and 143,100 are considered equivalent to the CBER 100,000 BAU/mL Standard, and between 6,990 and 14,310 for the CBER 10,000 BAU/mL Standard when assays are done in triplicate.

INDICATIONS AND USAGE

16, 17, 18, 20

Standardized glycerinated allergenic extracts in potencies of 10,000 BAU/mL and 100,000 BAU/mL are indicated for use in diagnosis and immunotherapy of patients presenting symptoms of allergy (hay fever, rhinitis, etc.) to specific grass pollens. Concentrated extracts must be diluted prior to use in intradermal testing and immunotherapy. The selection of allergenic extracts to be used should be based on a thorough and carefully taken history of hypersensitivity, and confirmed by skin testing. 27, 28 10,000 BAU/mL dose form should be used initially for percutaneous testing. If negative, the 100,000 BAU/mL dose can be used.
The use of mixed or unrelated antigens for skin testing is not recommended since, in the case of a positive reaction, it does not indicate which component of the mix is responsible for the reaction, while, in the case of a negative reaction, it fails to indicate whether the individual antigens at full concentration would give a positive reaction. Utilization of such mixes for compounding a treatment may result, in the former case, in administering unnecessary antigens and, in the latter case, in the omission of a needed allergen.
Allergens to which a patient is extremely sensitive should not be included in treatment mixes with allergens to which there is much less sensitivity, but should be administered separately. This allows individualized and better control of dosage increases, including adjustments in dosage becoming necessary after severe reactions which may occur to the highly reactive allergen. Note: BAU/mL Standardized grass pollens are not interchangeable with any other grass pollen products.

CONTRAINDICATIONS

There are no known absolute contraindications to immunotherapy. See PRECAUTIONS for pregnancy risks.
Patients with cardiovascular diseases or pulmonary diseases such as symptomatic unstable, steroid-dependent asthma, and/or those who are receiving cardiovascular drugs such as beta blockers, may be at higher risk for severe adverse reactions. These patients may also be more refractory to the normal allergy treatment regimen. Patients should be treated only if the benefit of treatment outweighs the risks.1
Any injections, including immunotherapy, should be avoided in patients with a bleeding tendency.
Since there are differences of opinion concerning the possibility of routine immunizations exacerbating autoimmune diseases, immunotherapy should be given cautiously to patients with autoimmune diseases, and only if the risk from exposure to the allergen is greater than the risk of exacerbating the autoimmune process.

WARNINGS

See WARNINGS at the beginning of this instruction sheet.

Allergenic extract should be temporarily withheld from patients or the dose adjusted downward if any of the following conditions exist: (1) severe symptoms of rhinitis and/or asthma; (2) infection or flu accompanied by fever; or (3) exposure to excessive amounts of clinically relevant allergen prior to a scheduled injection. Do not start immunotherapy during a period of symptoms due to exposure. Since the individual components of the extract are those to which the patient is allergic, and to which he or she will be exposed, typical allergic symptoms may follow shortly after the injection, particularly when the antigen load from exposure plus the injected antigen exceeds the patient's antigen tolerance. (4) Any evidence of a local or generalized reaction requires a reduction in dosage during the initial stages of immunotherapy, as well as during maintenance therapy.
THE CONCENTRATE SHOULD NOT BE INJECTED AT ANY TIME UNLESS TOLERANCE HAS BEEN ESTABLISHED. DILUTE CONCENTRATED EXTRACTS WITH STERILE ALBUMIN SALINE WITH PHENOL (0.4%) FOR INTRADERMAL TESTING.
INJECTIONS SHOULD NEVER BE GIVEN INTRAVENOUSLY. Subcutaneous injection is recommended. Intracutaneous or intramuscular injections may produce large local reactions or be excessively painful.
AFTER INSERTING NEEDLE SUBCUTANEOUSLY, BUT BEFORE INJECTING, ALWAYS WITHDRAW THE PLUNGER SLIGHTLY. IF BLOOD APPEARS IN THE SYRINGE, CHANGE NEEDLE AND GIVE THE INJECTION IN ANOTHER SITE.

BOXED WARNING

IF CHANGING TO A DIFFERENT LOT OF STANDARDIZED EXTRACT: Even though it is the same formula and concentration, the first dose of the new extract should not exceed 25% to 50% of the last administered dose from the previous extract.

IF THE STANDARDIZED EXTRACT PREVIOUSLY USED WAS FROM ANOTHER MANUFACTURER: Since manufacturing processes and sources of raw materials differ among manufacturers, the interchangeability of extracts from different manufacturers cannot be insured. The starting dose of the standardized glycerinated extract therefore should be greatly decreased even though the extract is the same formula and dilution. Initiate therapy as though patient had not been receiving immunotherapy, or determine initial dose by skin test using serial dilutions of the extract. In highly sensitive individuals, the skin test method may be preferable. See DOSAGE AND ADMINISTRATION and ADVERSE REACTIONS Sections.
IF A PROLONGED PERIOD OF TIME HAS ELAPSED SINCE THE LAST INJECTION: Patients may lose tolerance for allergen injections during prolonged periods between doses. The duration of tolerance is an individual characteristic and varies from patient to patient. In general, the longer the lapse in the injection schedule, the greater dose reduction required. If the interval since last dose is over four weeks, perform skin tests to determine starting dose.
IF THE PREVIOUS EXTRACT WAS OUTDATED: The dating period for allergenic extracts indicates the time that they can be expected to remain potent under refrigerated storage conditions (2°- 8°C). During the storage of extracts, even under ideal conditions, some loss of potency occurs. For this reason, extracts should not be used beyond their expiration date. If a patient has been receiving injections of an outdated extract, he may experience excessive local or systemic reactions when changed to a new, and possibly more potent extract. In general, the longer the material has been outdated, the greater the dose reduction necessary for the fresh extract.
IF THE PREVIOUS EXTRACT WAS NON-STANDARDIZED: Standardized extracts differ in potency from non-standardized extracts. Use Table 2 for guidance in selecting dose for switching. To confirm dose selected, side-by-side skin testing of new and old extracts can be carried out. (See CLINICAL PHARMACOLOGY, Table 2.) Initiate therapy as though the patient had not been receiving immunotherapy, or determine initial dose by skin test using serial dilutions of the extract. See PRECAUTIONS and DOSAGE AND ADMINISTRATION Sections below.
IF ANY OTHER CHANGES HAVE BEEN MADE IN THE EXTRACT CONCENTRATE FORMULA: Changes other than those listed above may include situations such as a redistribution of component parts or percentages, a difference in extracting fluid (i.e., change from non-glycerin extracts to 50% glycerin extracts), combining two or more stock concentrates, or any other change.
It should be recognized that any change in formula can affect a patient's tolerance of the treatment. The usual 1/2 of the previous dose for a new extract may produce an adverse reaction; extra dilutions are recommended whenever starting a revised formula. The greater the change, the greater the number of dilutions required.

WARNINGS

Proper selection of the dose and careful injection should prevent most systemic reactions. It must be remembered, however, that allergenic extracts are highly potent in sensitive individuals, and that systemic reactions of varying degrees of severity may occur, including urticaria, rhinitis, conjunctivitis, wheezing, coughing, angioedema, hypotension, bradycardia, pallor, laryngeal edema, fainting, or even anaphylactic shock and death. Patients should be informed of this, and the precautions should be discussed prior to immunotherapy. (See PRECAUTIONS below.) Severe systemic reactions should be treated as indicated in the ADVERSE REACTIONS Section below.

PRECAUTIONS

1. GENERAL

The presence of asthmatic signs and symptoms appear to be an indicator for severe reactions following allergy injections. An assessment of airway obstruction either by measurement of peak flow or an alternate procedure may provide a useful indicator as to the advisability of administering an allergy injection.1, 30, 31, 32, 33
Concentrated extracts must be diluted prior to use: See DOSAGE AND ADMINISTRATION Section for detailed instructions on the dilution of standardized glycerinated allergenic extracts.
Allergenic extracts diluted with Albumin Saline with Phenol (0.4%) may be more potent than extracts diluted with diluents which do not contain stabilizers. When switching from non-stabilized to stabilized diluent, consider weaker initial dilutions for both intradermal testing and immunotherapy.
Sterile solutions, vials, syringes, etc. should be used and aseptic precautions observed in making dilutions.
To avoid cross-contamination, do not use the same needle to withdraw materials from vials of more than one extract, or extract followed by diluent.
A sterile tuberculin syringe graduated in 0.01 mL units should be used to measure each dose from the appropriate dilution. Aseptic techniques should always be employed when injections of allergenic extracts are being administered.
A separate sterile syringe should be used for each patient to prevent transmission of hepatitis and other infectious agents from one person to another.
Patient reactions to previous injections should be reviewed before each new injection. A conservative dosage schedule should be followed by the physician until a pattern of local responses is established which can be used to monitor increases in dosage.
Rarely, a patient is encountered who develops systemic reactions to minute doses of allergen and does not demonstrate increasing tolerance to injections after several months of treatment. If systemic reactions or excessive local responses occur persistently at very small doses, efforts at immunotherapy should be stopped.
PATIENTS SHOULD BE OBSERVED IN THE OFFICE FOR AT LEAST 30 MINUTES AFTER EACH TREATMENT INJECTION. Most severe reactions will occur within this time period, and rapid treatment measures should be instituted. See ADVERSE REACTIONS Section for such treatment measures.

2. INFORMATION FOR PATIENTS

Patients should be instructed in the recognition of adverse reactions to immunotherapy, and in particular, to the symptoms of shock. Patients should be made to understand the importance of a 30 minute observation period, and be warned to return to the office promptly if symptoms occur after leaving.

3. CARCINOGENESIS, MUTAGENESIS, IMPAIRMENT OF FERTILITY

Long-term studies in animals have not been conducted with allergenic extracts to determine their potential for carcinogenicity, mutagenicity or impairment of fertility.

4. PREGNANCY

29

Allergenic Extracts. Animal reproduction studies have not been conducted with allergenic extracts. It is also not known whether allergenic extracts can cause fetal harm when administered to a pregnant woman or can affect reproduction capacity. Allergenic extracts should be given to a pregnant woman only if clearly needed. For women who have been getting maintenance doses of allergen without side effect, the occurrence of pregnancy is not an indication to stop immunotherapy.

5. NURSING MOTHERS

There are no current studies on secretion of the allergenic extract components in human milk, or of their effect on the nursing infant. Because many drugs are excreted in human milk, caution should be exercised when allergenic extracts are administered to a nursing woman.

6. PEDIATRIC USE

Since dosage for the pediatric population is the same as for adults,21 the larger volumes of solution may produce excessive discomfort. Therefore, in order to achieve the total dose required, the volume of the dose may need to be divided into more than one injection per visit.

7. GERIATRIC USE

The reactions from immunotherapy can be expected to be the same in elderly patients as in younger ones. Elderly patients may be more likely to be on medication that could block the effect of epinephrine which could be used to treat serious reactions, or they could be more sensitive to the cardiovascular side effect of epinephrine because of pre-existing cardiovascular disease.4

8. DRUG INTERACTIONS

Patients on non-selective beta blockers may be more reactive to allergens given for diagnosis or treatment, and may be unresponsive to the usual doses of epinephrine used to treat allergic reactions.19
Certain medications may lessen the skin test wheal and erythema responses elicited by allergens and histamine for varying time periods. Conventional antihistamines should be discontinued at least 5 days before skin testing. Long acting antihistamines should be discontinued for at least 3 weeks prior to skin testing.23 Topical steroids should be discontinued at the skin test site for at least 2-3 weeks before skin testing.23, 24 Tricyclic antidepressants such as Doxepin should be withheld for at least 7 days before skin testing.25 Topical local anesthetics may suppress the flare responses and should be avoided in skin test sites.26

ADVERSE REACTIONS

1. Local Reactions
Some erythema, swelling or pruritus at the site of injection are common, the extent varying with the patient. Such reactions should not be considered significant unless they persist for at least 24 hours. Local reactions (erythema or swelling) which exceed 4-5 cm in diameter are not only uncomfortable, but also indicate the possibility of a systemic reaction if dosage is increased. In such cases the dosage should be reduced to the last level not causing the reaction and maintained at this level for two or three treatments before cautiously increasing again.
Large persistent local reactions may be treated by local cold, wet dressings and/or the use of oral antihistamines. They should be considered a warning of possible severe systemic reactions and an indication of the need for temporarily reduced dosages.
A mild burning immediately after the injection is to be expected. This usually leaves in 10 to 20 seconds.

2. Systemic Reactions
With careful attention to dosage and administration, systemic reactions occur infrequently, but it cannot be overemphasized that in sensitive individuals, any injection could result in anaphylactic shock. Therefore, it is imperative that physicians administering allergenic extracts understand and be prepared for the treatment of severe reactions.
Other possible systemic reactions which may occur in varying degrees of severity are laryngeal edema, fainting, pallor, bradycardia, hypotension, angioedema, cough, wheezing, conjunctivitis, rhinitis, and urticaria. Adverse reaction frequency data for allergenic extract administration for testing and treatment show that risk is low.1, 22
If a systemic or anaphylactic reaction does occur, apply a tourniquet above the site of injection and inject 1:1,000 epinephrine-hydrochloride intramuscularly or subcutaneously into the opposite arm. Loosen the tourniquet at least every 10 minutes. Do not obstruct arterial blood flow with the tourniquet.
EPINEPHRINE DOSAGE
ADULT DOSAGE: 0.3 to 0.5 mL should be injected. Repeat in 5 to 10 minutes if necessary.
PEDIATRIC DOSAGE: The usual initial dose is 0.01 mg (mL) per kg body weight or 0.3 mg (mL) per square meter of body surface area. Suggested dosage for infants to 2 years of age is 0.05 to 0.1 mL; for children 2 to 6 years, 0.15 mL; and children 6 to 12 years, 0.2 mL. Single pediatric doses should not exceed 0.3 mg (mL). Doses may be repeated as frequently as every 20 minutes, depending on the severity of the condition and the response of the patient.
After administration of epinephrine, profound shock or vasomotor collapse should be treated with intravenous fluids, and possibly vasoactive drugs. Airway patency should be insured. Oxygen should be given by mask. Intravenous antihistamines, inhaled bronchodilators, theophylline and/or corticosteroids may be used if necessary after adequate epinephrine and circulatory support have been given. Emergency resuscitation measures and personnel trained in their use must be available immediately in the event of a serious systemic or anaphylactic reaction not responsive to the above measures
[Ref. J.Allergy and Clinical Immunology, 77(2): p. 271-273, 1986].
Rarely are all of the above measures necessary; the tourniquet and epinephrine usually produce prompt responses. However, the physician should be prepared in advance for all contingencies. Promptness in beginning emergency treatment measures is of utmost importance.
Severe systemic reactions mandate a decrease of at least 50% in the next dose, followed by cautious increases. Repeated systemic reactions, even of a mild nature, are sufficient reason for the cessation of further attempts to increase the reaction-causing dose.

3. Adverse Event Reporting
Report all adverse events to Jubilant HollisterStier LLC Customer Technical Services Department at 1 (800) 992-1120. A voluntary adverse event reporting system for health professionals is available through the FDA MEDWATCH program. Preprinted forms (FDA Form 3500) are available from the FDA by calling 1 (800) FDA-1088. Completed forms should be mailed to MEDWATCH, 5600 Fisher Lane, Rockville, MD 20852-9787 or Fax to: 1 (800) FDA-0178.

OVERDOSAGE

See ADVERSE REACTIONS Section.

DOSAGE AND ADMINISTRATION

1. General

Sterile aqueous diluent containing albumin (human) [Albumin Saline with Phenol (0.4%)] or diluent of 50% glycerin may be used when preparing dilutions of the concentrate for immunotherapy. For intradermal testing dilutions, Albumin Saline with Phenol (0.4%) is recommended.
Dilutions should be made accurately and aseptically, using sterile diluent, vials, syringes, etc. Mix thoroughly and gently by rocking or swirling.
Parenteral drug products should be inspected visually for particulate matter and discoloration prior to administration whenever solution and container permit.

2. Diagnosis
Prick or Puncture Test: To identify highly sensitive individuals and as a safety precaution, it is recommended that a prick or puncture test using a drop of 10,000 BAU/mL extract be performed prior to initiating intradermal testing. If this test is negative, a second prick/puncture test may be performed using a 100,000 BAU/mL extract. Prick tests are performed by placing a drop of extract on the skin and piercing through the drop into the skin with a slight lifting motion. Puncture tests are performed by placing a drop of extract concentrate on the skin and piercing the skin through the drop with a small needle such as a Prick Lancetter. Fifteen minutes after puncture is made the diameter of wheal and erythema reactions are measured, and the sensitivity class of the patient determined by Table 3. Less sensitive individuals (Class 0 to 1+) can be tested intradermally with the recommended dilutions of the extract concentrate (See intradermal testing instructions).
Intradermal Test: Patients with a negative prick or puncture test should be tested intradermally with 100 BAU/mL. If this test is negative, a second intradermal test may be performed using a 1,000 BAU/mL extract. The negative control should have glycerin concentration equivalent to the glycerin concentration of the intradermal test solution, not to exceed 5% glycerin.
It is recommended that patients be tested using the intradermal technique only after screening by prick or puncture test.
Extract for intradermal testing should be prepared by diluting the stock concentrate, provided in multiple-dose vials, with Sterile Albumin Saline with Phenol (0.4%) (refer to Table 4 in the Immunotherapy section below).
To administer the intradermal strength dilutions, a 1 mL tuberculin syringe with a short 27-gauge needle should be used. The needle is inserted intradermally at a 30° angle, bevel down, and 0.02 to 0.05 mL of the extract is injected. Fifteen minutes following injection, the diameter of wheal and erythema reactions are measured, and the patient's sensitivity class is determined by the table below. Skin tests are graded in terms of the wheal and erythema response noted at 10 to 20 minutes. Wheal and erythema size may be recorded by actual measurement of the extent of both responses. Refer to Table 3 to determine the skin test sensitivity class. The corresponding ∑E (sum of the longest diameter and the mid-point orthogonal diameters of erythema) is also presented.

TABLE 3 Classification of Skin Test Sensitivity for Intradermal and Pick or Puncture

Class | Wheal Diameter | Erythema Diameter | Corresponding ∑E
0 | < 5 mm | <5 mm | <10 mm
± | 5-10 mm | 5-10 mm | 10-20 mm
1+ | 5-10 mm | 11-20 mm | 20-40 mm
2+ | 5-10 mm | 21-30 mm | 40-60 mm
3+ | 10-15 mm a | 31-40 mm | 60-80 mm
4+ | >15 mm b | >40 mm | >80 mm

a. or with pseudopods

b. or with many pseudopods

3. Immunotherapy
Allergenic extracts should be administered using a sterile syringe with 0.01 mL gradations and a 25-27 gauge X 1/2" to 5/8" needle. The injections are given subcutaneously. The most common sites of injection are the lateral aspect of the upper arm or thigh. Intracutaneous or intramuscular injections may produce large local reactions which may be very painful.
Dosage of allergenic extracts is a highly individualized matter and varies according to the degree of sensitivity of the patient, his clinical response, and tolerance to the extract administered during the early phases of an injection regimen. The starting dose should be based on skin tests of the extract to be used for immunotherapy. To prepare dilutions for intradermal and therapeutic use, make a 1:10 dilution by adding 1.0 mL of the concentrate to 9.0 mL of Sterile Albumin Saline with Phenol (0.4%). Subsequent serial dilutions are made in a similar manner. (See Table 4.) To determine the starting dose, begin intradermal testing with the most dilute extract preparation. Inject 0.02 mL and read the reaction after 15 minutes. Intradermal testing is continued with increasing concentrations of the extract until a reaction of 11-20 mm erythema ∑E 20-40 mm) and/or a 5 mm wheal occurs. This concentration at a dose of 0.03 mL then can serve as a starting dose for immunotherapy and be increased by 0.03 mL to as high as 0.12 mL increments each time until 0.3 mL is reached, at which time a dilution 10 times as strong can be used, starting with 0.03 mL. Proceed in this way until a tolerance dose is reached or symptoms are controlled. Suggested maintenance dose is 0.2 mL of the concentrate. Occasionally, higher doses are necessary to relieve symptoms. Special caution is required in administering doses greater than 0.2 mL. The interval between doses normally is 3 to 7 days.
Potencies of 10,000 BAU/mL and 100,000 BAU/mL are available for treatment. The two selections are available to facilitate safe switching by providing flexibility in dosing. For previously untreated patients, initiate treatment using dilutions made from the 10,000 BAU/mL concentrate. If tolerated and symptoms justify a higher dosage, then use of dilutions made from the 100,000 BAU/mL concentrate is warranted. Proceed with caution when using 100,000 BAU/mL in higher doses.
When converting a patient who is currently receiving non-standardized grass pollen extracts, it is recommended that skin testing be performed to compare the potency of the new and old extracts. If you choose not to skin test as recommended, but to continue therapy, the maximum first dose of the new allergenic product should not exceed 10% (1/10) of the previous dose.
This is offered as a suggested schedule for average patients and will be satisfactory in most cases. However, the degree of sensitivity varies in many patients. The size of the dose should be adjusted and should be regulated by the patient's tolerance and reaction. The size of the dose should be decreased if the previous injection resulted in marked local or the slightest general reaction. Another dose should never be given until all local reactions resulting from the previous dose have disappeared.
In some patients, the dosage may be increased more rapidly than called for in the schedule. In seasonal allergies, treatment should be started and the interval between doses regulated so that at least the first twenty doses will have been administered by the time symptoms are expected. Thus, the shorter the interval between the start of immunotherapy and the expected onset of symptoms, the shorter the interval between each dose. Some patients may even tolerate daily doses. A maintenance dose, the largest dose tolerated by the patient that relieves symptoms without producing undesirable local or general reactions, is recommended for most patients. The upper limits of dosage have not been established; however, doses larger than 0.2 mL of the glycerin concentrate may be painful due to the glycerin content. The dosage of allergenic extract does not vary significantly with the respiratory allergic disease under treatment. The size of this dose and the interval between doses will vary and can be adjusted as necessary. Should symptoms develop before the next injection is scheduled, the interval between doses should be decreased. Should allergic symptoms or local reactions develop shortly after the dose is administered, the size of the dose should be decreased. In seasonal allergies, it is often advisable to decrease the dose to one-half or one-quarter of the maximum dose previously attained if the patient has any seasonal symptoms.
The interval between maintenance doses can be increased gradually from one week to 10 days, to two weeks, to three weeks, or even to four weeks if tolerated. Repeat the doses at a given interval three or four times to check for untoward reactions before further increasing the interval. Protection is lost rapidly if the interval between doses is more than four weeks. (See WARNINGS Section.)
The usual duration of treatment has not been established. A period of two or three years of injection therapy constitutes an average minimum course of treatment.

TABLE 4
TEN-FOLD DILUTION SERIES
Standardized Extracts Labeled 100,000 BAU/mL
Dilution | Extract | + Diluent | = | BAU/mL Concentration
0 | Concentrate | +0 mL | = | 100,000
1 | 1 mL Concentrate | +9 mL | = | 10,000
2 | 1 mL dilution #1 | +9 mL | = | 1,000
3 | 1 mL dilution #2 | +9 mL | = | 100
4 | 1 mL dilution #3 | +9 mL | = | 10
5 | 1 mL dilution #4 | +9 mL | = | 1.0
6 | 1 mL dilution #5 | +9 mL | = | 0.10
7 | 1 mL dilution #6 | +9 mL | = | 0.010

(4) PEDIATRIC USE

The dose for the pediatric population is the same as for adults. (See PRECAUTIONS.)

(5) GERIATRIC USE

The dose for elderly patients is the same as for adult patients under 65.4

HOW SUPPLIED

Standardized allergenic extracts of grass pollens are supplied for diagnostic and therapeutic use:

Diagnostics:
Extracts: Pollens*
Prick/puncture tests, 10,000 BAU/mL and 100,000 BAU/mL [50% glycerin (v/v)] in 5 mL dropper vial.
Intradermal Tests [Aqueous] of 100 BAU/mL in 5 mL vial, and 1,000 BAU/mL in 5 mL vial.
(Intradermal test solutions may contain up to 5% glycerin.)
*Bermuda grass, 10,000 BAU/mL is highest concentration.
Bulk Therapeutics [50% glycerin (v/v)] in multiple dose vials:
Extracts: Pollens*
10 mL vial, in strengths of 100,000 BAU/mL and 10,000 BAU/mL
30 mL vial, in strengths of 100,000 BAU/mL and 10,000 BAU/mL
50 mL vial, in strengths of 100,000 BAU/mL and 10,000 BAU/mL
*Bermuda grass, 10,000 BAU/mL only.

STORAGE

The expiration date of pollen extract in 50% glycerin is listed on the container label. The extract should be stored at 2°- 8°C. Dilutions containing less than 50% glycerin are less stable and, if loss of potency is suspected, should be checked by skin testing with equal units of a freshly prepared dilution on known pollen allergic individuals. The expiration date of the intradermal tests is listed on container labels. Store at 2°- 8°C.

LIMITED WARRANTY

A number of factors beyond our control could reduce the efficacy of this product or even result in an ill effect following its use. These include storage and handling of the product after it leaves our hands, diagnosis, dosage, method of administration and biological differences in individual patients. Because of these factors, it is important that this product be stored properly and that the directions be followed carefully during use. No warranty, express or implied, including any warranty of merchantability or fitness, is made. Representatives of the Company are not authorized to vary the terms or the contents of any printed labeling, including the package insert, for this product except by printed notice from the Company's headquarters. The prescriber and user of this product must accept the terms hereof.

REFERENCES

1. Lockey, Richard F., Linda M. Benedict, Paul C. Turkeltaub, Samuel C. Bukantz. Fatalities from immunotherapy (IT) and skin testing (ST). J. Allergy Clin. Immunol., 79 (4): 660-677, 1987.
2. U.S. Food and Drug Administration (FDA), Center for Biologics Evaluation and Research (CBER). ELISA competition assay (Enzyme-linked Immunosorbent Assay). Methods of Allergenic Products Testing Laboratory. October 1993. CBER Docket No. 94N.0012.
3. U.S. Food and Drug Administration, Center for Biologics Evaluation and Research, Data on file.
4. Peebles, Ray Stokes, Jr., B. Bochner, Howard J. Zeitz, ed. Anaphylaxis in the elderly. Immunology and Allergy Clinics of North America. 13 (3): 627-646, August 1993.
5. Turkeltaub, P., S. Rastogi. Quantitative intradermal test procedure for evaluation of subject sensitivity to standardized allergenic extracts and for assignment of bioequivalent allergy units to reference preparations using the ID50EAL method, Allergenic Products Testing Laboratory, Center for Biologics Evaluation and Research (CBER), FDA. Revised November 1994.
6. Lowell, F. C., W. Franklin. A "double-blind" study of treatment with aqueous allergenic extracts in cases of allergic rhinitis. J. Allergy, 34 (2): 165-182, 1983.
7. Lowell, F. C., W. Franklin. A double-blind study of the effectiveness and specificity of injection therapy in ragweed hay fever. N. Eng. J. Med., 273 (13): 675-679, 1965.
8. Zavazal, V., A. Stajner. Immunologic changes during specific treatment of the atopic state. II. Acta. Allergol., 25 (1): 11-17, 1970.
9. Reisman, R.E., J.I. Wypych, E.E. Arbesman. Relationship of immunotherapy, seasonal pollen exposure and clinical response to serum concentrations of total IgE and ragweed-specific IgE. Int. Arch. Allergy Appl. Immunol., 48 (6): 721-730, 1975.
10. Taylor, W.W., J.L. Ohman, F. C. Lowell. Immunotherapy in cat-induced asthma; double-blind trial with evaluation of bronchial responses to cat allergen and histamine. J. Allergy and Clin. Immunol., 61 (5): 283-287, 1978.
11. Smith, A. P. Hyposensitization with Dermatophagoides pteronyssinus antigen: trial in asthma induced by house dust. Br. Med. J., 4: 204-206, 1971.
12. Chapman, M.D., T.A.E. Platts-Mills, M. Gabriel, H.K. Ng, W. G. L. Allen, L. E. Hill, A. J. Nunn. Antibody response following prolonged hyposensitization with Dermatophagoides pteronyssinus extract. Int. Arch. Allergy Appl. Immunol., 61: 431-440, 1980.
13. Norman, P.S. Postgraduate Course Presentation. An overview of immunotherapy, implications for the future. J. Allergy Clin. Immunol., 65 (2): 87-96, 1980.
14. Norman, P.S., W. L. Winkenwerder. Maintenance immunotherapy in ragweed hay fever. J. Allergy, 74: 273-282, 1971.
15. Norman, P.S., W. L. Winkenwerder, L. M. Lichtenstein. Immunotherapy of hay fever with ragweed antigen E; comparisons with whole pollen extract and placebos. J. Allergy, 42: 93-108, 1968.
16. Sheldon, J. M., R. G. Lovell, K. P. Matthews. A Manual of Clinical Allergy. Second Edition. W.B. Saunders, Philadelphia, 1967, pp. 107-112.
17. Sherman, W. B. Hypersensitivity mechanism and management. W. B. Sanders, Philadelphia, 1968, pp. 169-172.
18. Swineford, O. Asthma and Hay Fever. Charles C. Thomas, Springfield, IL, 1971, pp. 148-155.
19. Jacobs, R. L., G. W. Rake, Jr., et al. Potentiated anaphylaxis in patients with drug-induced beta-adrenergic blockade. J. Allergy and Clin. Immunol., 68 (2): 125-127, August 1981.
20. Patterson, Roy, et al. Allergy Principles and Practice, 2nd ed. E. Middleton, Jr., C.E. Reed, E.F. Ellis, Ed., C.V. Mosby Co., 1983, St. Louis, MO, 1983, Chapter 52.
21. Levy, D.A., L.M. Lichtenstein, E.O. Goldstein, and K. Ishizaka. Immunologic and cellular changes accompanying the therapy of pollen allergy. J. Clinical Investigation, 50:360, 1971.
22. Turkeltaub, Paul C., MD, and Peter J. Gergen, MD. The risk of adverse reactions from percutaneous prick-puncture allergen skin testing, venipuncture, and body measurements: data from the Second National Health and Nutrition Examination Survey, 1976-80 (NHANES II). J. Allergy Clin. Immunol. 84(6): 886-890, Dec. 1989.
23. Pipkorn, Ulf. Pharmacological influence of anti-allergic medication on In Vivo allergen testing. Allergy. 43: 81-86, 1988.
24. Andersson, M. and U. Pipkorn. Inhibition of the dermal immediate allergic reaction through prolonged treatment with topical glucocorticosteroids. J. Allergy Clin. Immunol. 79 (2): 345-349, Feb. 1987.
25. Rao, Kamineni S., et al. Duration of suppressive effect of tricyclic anti-depressants on histamine induced wheal and flare reactions on human skin. J. Allergy Clin. Immunol. 82: 752-757, November 1988.
26. Pipkorn, Ulf, and M. Andersson. Topical dermal anesthesia inhibits the flare but not the wheal response to allergen and histamine in the skin prick test. Clinical Allergy. 17: 307-311, 1987.
27. Pauli, G., J.C. Bessot, R. Thierry and A. Lamensons. Correlation between skin, inhalation tests and specific IgE in a study of 120 subjects to house dust and D. pteronyssinus. Clin. Allergy. 7:337, 1977.
28. Murray, A.B., A.C. Ferguson and B.J. Morrison. Diagnosis of house dust mite allergy in asthamatic children. What constitutes positive history? J. Allergy Clin. Immunol. 71: 21, 1983.
29. Metzger, W.J., E. Turner and R. Patterson. The safety of immunotherapy during pregnancy. J. Allergy Clin. Immunol. 61 (4): 268-272, 1978.
30. Reid, M.J., R.F. Lockey, P.C. Turkletaub, T.A.E. Platts-Mills. Survey of fatalities from skin testing and immunotherapy. J. Allergy Clin. Immunol. 92 (1): 6-15, July 1993.
31. Reid, M.J., G. Gurka. Deaths associated with skin testing and immunotherapy. J. Allergy Clin. Immunol. 97(1) Part 3:231, Abstract 195, January 1996.
32. Thompson, R.A. et al, report of a WHO/IUIS working group. The current status of allergen immunotherapy (hyposensitization). Allergy. 44: 369-379, 1989.
33. Malling, H.-J., B. Weeke, et al, The European Academy of Allergology and Clinical Immunology. Position Papers. Allergy. 48 (Supplement 14): 9-82, 1993.